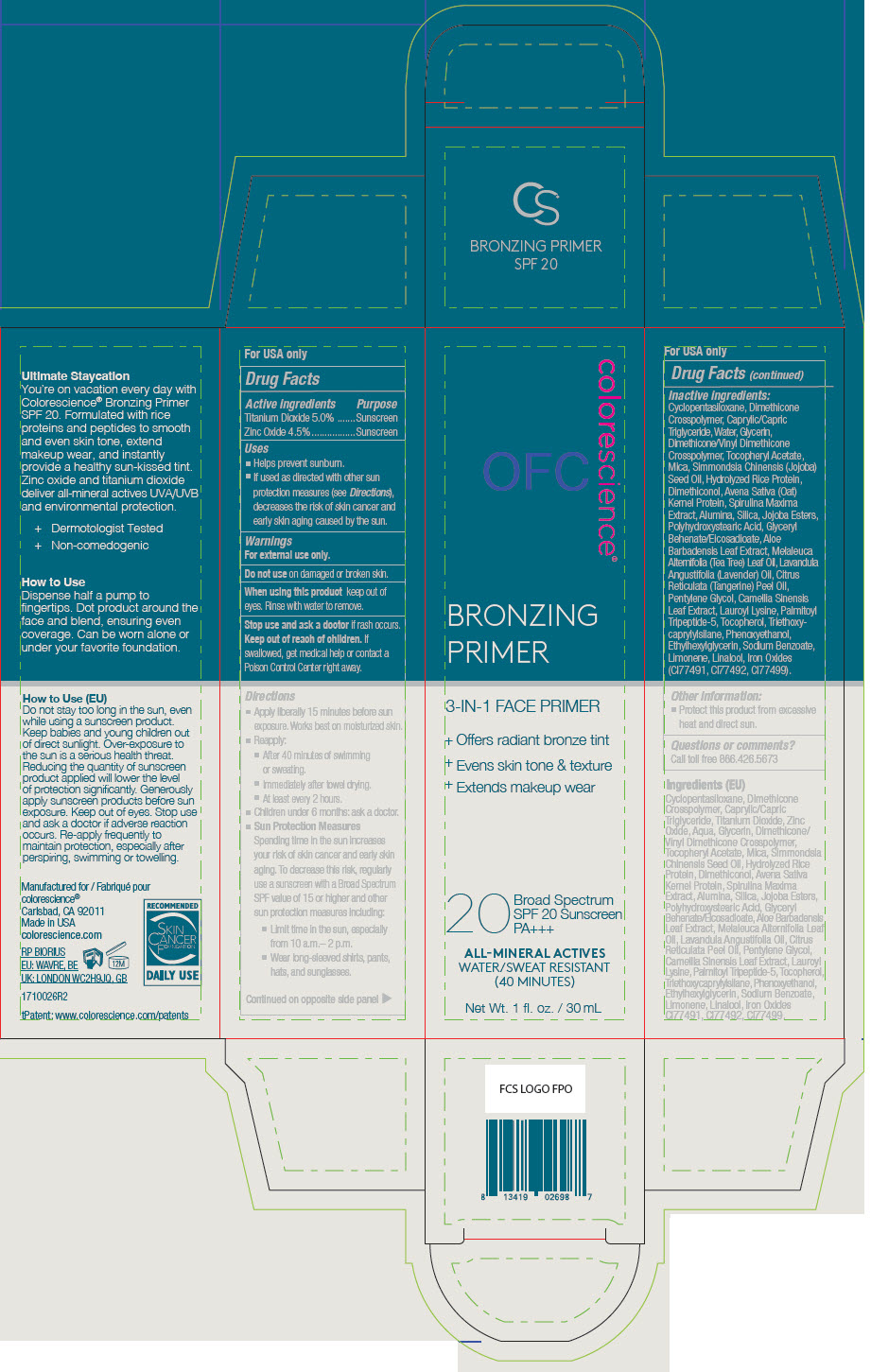 DRUG LABEL: Bronzing Primer SPF 20
NDC: 68078-045 | Form: LIQUID
Manufacturer: Colorescience
Category: otc | Type: HUMAN OTC DRUG LABEL
Date: 20251217

ACTIVE INGREDIENTS: TITANIUM DIOXIDE 50 mg/1 mL; ZINC OXIDE 4.5 mg/1 mL
INACTIVE INGREDIENTS: CYCLOMETHICONE 5; DIMETHICONE CROSSPOLYMER; MEDIUM-CHAIN TRIGLYCERIDES; WATER; GLYCERIN; DIMETHICONE, UNSPECIFIED; .ALPHA.-TOCOPHEROL ACETATE; MICA; JOJOBA OIL; DIMETHICONOL (100000 CST); OAT; ARTHROSPIRA MAXIMA; ALUMINUM OXIDE; SILICON DIOXIDE; POLYHYDROXYSTEARIC ACID (2300 MW); GLYCERYL BEHENATE/EICOSADIOATE; ALOE VERA LEAF; TEA TREE OIL; LAVENDER OIL; MANDARIN OIL; PENTYLENE GLYCOL; GREEN TEA LEAF; LAUROYL LYSINE; PALMITOYL TRIPEPTIDE-5; TOCOPHEROL; PHENOXYETHANOL; ETHYLHEXYLGLYCERIN; SODIUM BENZOATE; LIMONENE, (+)-; LINALOOL, (+/-)-; TRIETHOXYCAPRYLYLSILANE; FERRIC OXIDE RED; FERRIC OXIDE YELLOW; FERROSOFERRIC OXIDE; HYDROLYZED RICE PROTEIN (ENZYMATIC; 2000 MW); GERANIOL; LINALYL ACETATE; LAVANDIN OIL

Bronzing Primer SPF 20

Drug Facts

ACTIVE INGREDIENT

Active ingredients | Purpose
Titanium Dioxide 5.0% | Sunscreen
Zinc Oxide 4.5% | Sunscreen

Uses

- Helps prevent sunburn.
- If used as directed with other sun protection measures (see Directions), decreases the risk of skin cancer and early skin aging caused by the sun.

Warnings

For external use only.

Do not use on damaged or broken skin.

When using this product keep out of eyes. Rinse with water to remove.

Stop use and ask a doctor if rash occurs.

Keep out of reach of children. If swallowed, get medical help or contact a Poison Control Center right away.

Directions

- Apply liberally 15 minutes before sun exposure. Works best on moisturized skin.
- Reapply:
  - After 40 minutes of swimming or sweating.
  - Immediately after towel drying.
  - At least every 2 hours.
- Children under 6 months: ask a doctor.
- Sun Protection Measures
  Spending time in the sun increases your risk of skin cancer and early skin aging. To decrease this risk, regularly use a sunscreen with a Broad Spectrum SPF value of 15 or higher and other sun protection measures including:
  - Limit time in the sun, especially from 10 a.m.– 2 p.m.
  - Wear long-sleeved shirts, pants, hats, and sunglasses.

Inactive ingredients

Cyclopentasiloxane, Dimethicone Crosspolymer, Caprylic/Capric Triglyceride, Water, Glycerin, Dimethicone/Vinyl Dimethicone Crosspolymer, Tocopheryl Acetate, Mica, Simmondsia Chinensis (Jojoba) Seed Oil, Hydrolyzed Rice Protein, Dimethiconol, Avena Sativa (Oat) Kernel Protein, Spirulina Maxima Extract, Alumina, Silica, Jojoba Esters, Polyhydroxystearic Acid, Glyceryl Behenate/Eicosadioate, Aloe Barbadensis Leaf Extract, Melaleuca Alternifolia (Tea Tree) Leaf Oil, Lavandula Angustifolia (Lavender) Oil, Citrus Reticulata (Tangerine) Peel Oil, Pentylene Glycol, Camellia Sinensis Leaf Extract, Lauroyl Lysine, Palmitoyl Tripeptide-5, Tocopherol, Triethoxycaprylylsilane, Phenoxyethanol, Ethylhexylglycerin, Sodium Benzoate, Limonene, Linalool, Iron Oxides (CI77491, CI77492, CI77499).

Other information

- Protect this product from excessive heat and direct sun.

Questions or comments?

Call toll free 866.426.5673

PRINCIPAL DISPLAY PANEL - 30 mL Bottle Carton

colorescience®

BRONZING
PRIMER

3-IN-1 FACE PRIMER

+ Offers radiant bronze tint
+ Evens skin tone & texture
+ Extends makeup wear

20
Broad Spectrum
SPF 20 Sunscreen
PA+++

ALL-MINERAL ACTIVES
WATER/SWEAT RESISTANT
(40 MINUTES)

Net Wt. 1 fl. oz. / 30 mL